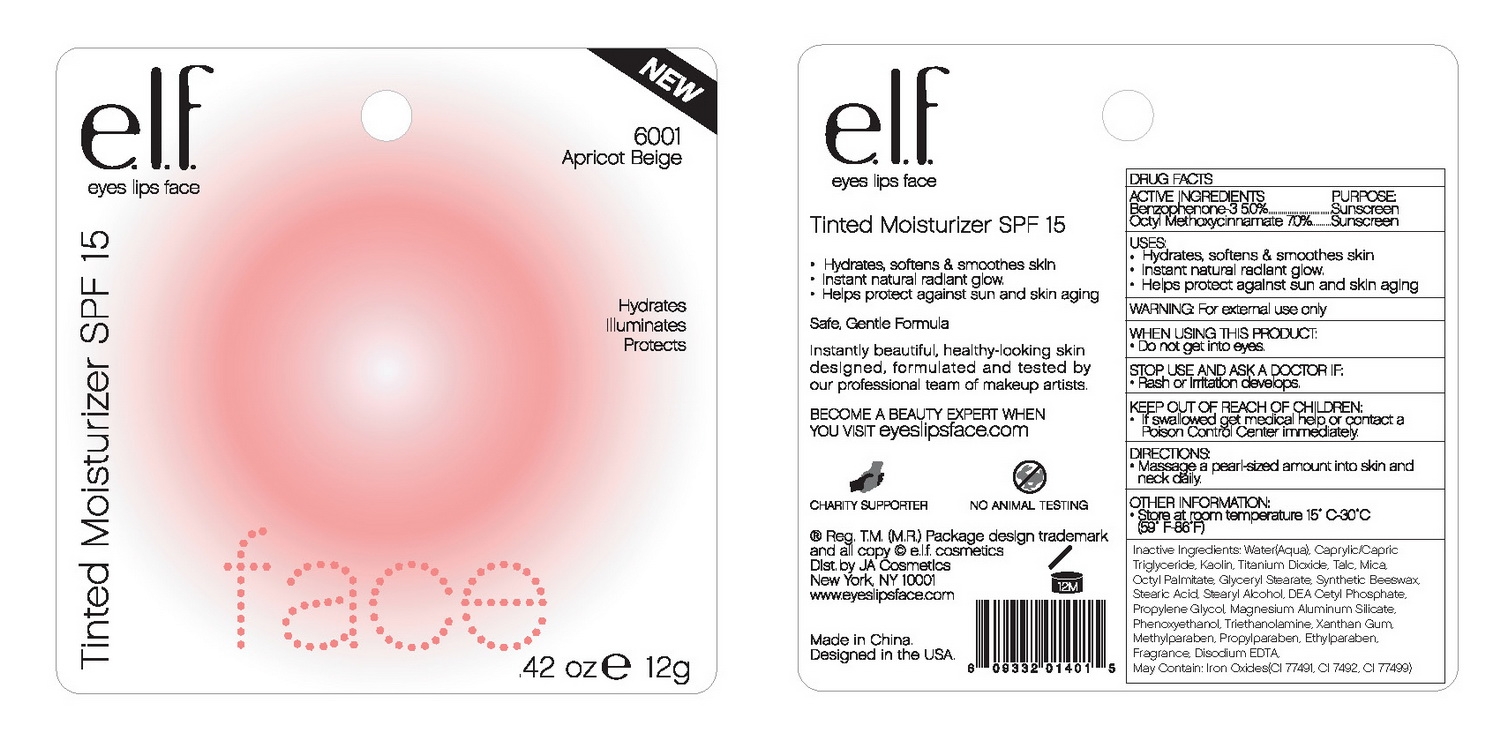 DRUG LABEL: ELF Tinted Moisturizer SPF 15
NDC: 52664-003 | Form: CREAM
Manufacturer: Hangzhou Facecare Cosmetics Co., Ltd.
Category: otc | Type: HUMAN OTC DRUG LABEL
Date: 20101117

ACTIVE INGREDIENTS: OXYBENZONE 5 g/100 g; OCTINOXATE 7 g/100 g
INACTIVE INGREDIENTS: MEDIUM-CHAIN TRIGLYCERIDES; TITANIUM DIOXIDE; MICA; METHYLPARABEN; PROPYLPARABEN; KAOLIN; FERRIC OXIDE RED; FERRIC OXIDE YELLOW; FERROSOFERRIC OXIDE; TALC; ETHYLHEXYL PALMITATE; GLYCERYL MONOSTEARATE; WHITE WAX; STEARIC ACID; STEARYL ALCOHOL; DIETHANOLAMINE CETYL PHOSPHATE; PROPYLENE GLYCOL; MAGNESIUM ALUMINUM SILICATE; PHENOXYETHANOL; TROLAMINE; XANTHAN GUM; ETHYLPARABEN; EDETATE DISODIUM; WATER 42.35 g/100 g

Drug Fact

Active Ingredient:

Benzophenone-3: 5.0%

Octyl Methoxycinnamate: 7.0%

Purpose:

Sunscreen

Uses:

- Hydrates, softens and smooths skin
- Instant natural radiant glow
- Helps protect against sun and skin aging

Warning:

For external use only

When Using This Product:

Do not get into eyes

Stop Use And Ask A Doctor If:

Rash or irritation develops and lasts

Keep Out of Reach Of Children:

If swallowed get medical help or contact a Poison Control Center immediately

Directions:

Massage a pearl-sized amount into skin and neck daily.

Other Information:

Store at room temperature 15-30C (59-86F)

Inactive Ingredient:

Water, Caprylic/Capric Triglyceride, Kaolin, Titanium Dioxide, Talc, Mica, Octyl Palmitate, Glyceryl Stearate, Synthetic Beeswax, Stearic Acid, Stearyl Alcohol, DEA-Cetyl Phosphate, Propylene Glycol, Magnesium Aluminum Silicate, Phenoxyehtanol, Triethanolamine, Xanthan Gum, Fragrance, Methylparaben, Propylparaben, Ethylparaben, Disodium EDTA.

May contain:

Iron Oxides (CI 77491, CI 77492, CI 77499)

PACKAGE LABEL

labe